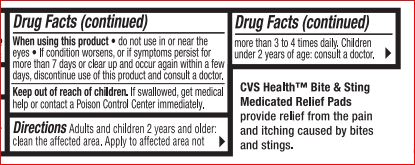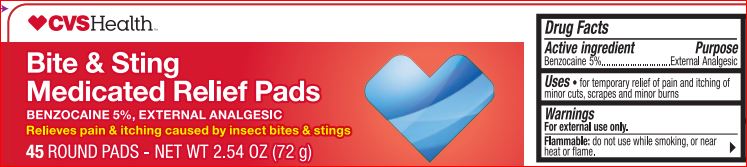 DRUG LABEL: Bite and Sting Medicated Relief Pads
NDC: 69842-856 | Form: LIQUID
Manufacturer: CVS
Category: otc | Type: HUMAN OTC DRUG LABEL
Date: 20180223

ACTIVE INGREDIENTS: BENZOCAINE 5 g/100 g
INACTIVE INGREDIENTS: ALOE VERA LEAF; ASCORBIC ACID; CAMPHOR (SYNTHETIC); CHAMOMILE; Cholecalciferol; Diisopropyl Adipate; CLOVE OIL; PEPPERMINT OIL; Octyldodecanol; OLIVE OIL; PEG-8 Dimethicone; Propylene Glycol; PYRIDOXINE HYDROCHLORIDE; VITAMIN A PALMITATE; Alcohol; SILICON DIOXIDE; Sodium Propoxyhydroxypropyl Thiosulfate Silica; .ALPHA.-TOCOPHEROL ACETATE; CORN OIL

Drag Facts

Active ingredient Purpose

Benzocaine - 5.00% Pain Relief

Uses

For temporarily relief of pain and itching associated with minor cuts, scrapes and minor burns

Warnings For external use only

Flammable: do not use while smoking or near heat or flame

When using this product

- avoid contact with eyes
- use only as directed

Stop use and ask a doctor if

• condition worsens
• symptoms last more than 7 days or clear up and occur again within a few days

Keep out of reach of the children
In case of accidental ingestion, seek professional or contact a Poison Control Center immediately.

Direction

• adults and children 2 years of age and older: Apply to affected area, not more than 3 to 4 times daily
• children under 2 years of age: Ask a doctor

Inactive ingredients

Aloe Barbadensis Leaf Juice, Ascorbic Acid, Camphor, Chamomilla Recutita (Matricaria) Flower Extract, Cholecalciferol, Diisopropyl Adipate,
Eugenia Caryophyllus (Clove) Flower Oil, Fragrance, Mentha Piperita (Peppermint) Oil, Octyldodecanol, Olea Europaea (Olive) Fruit Oil,
PEG-8 Dimethicone, Propylene Glycol, Pyridoxine HCl, Retinyl Palmitate, SD Alcohol 40, Silica, Sodium Propoxyhydroxypropyl Thiosulfate Silica,
Tocopheryl Acetate, Zea Mays (Corn) Oil